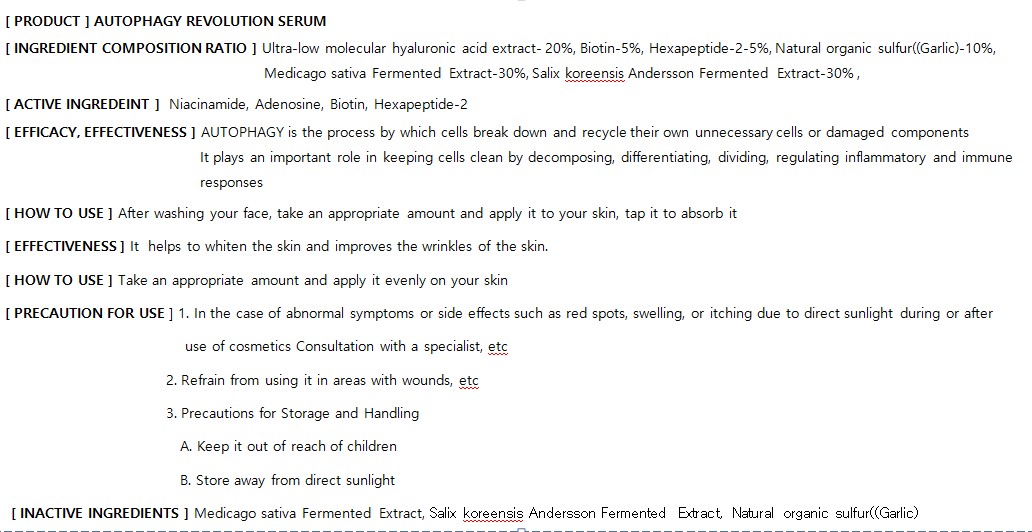 DRUG LABEL: AUTOPHAGY REVOLUTION SERUM
NDC: 82237-0006 | Form: LIQUID
Manufacturer: NFC LIFE SCIENCE CO.,LTD
Category: otc | Type: HUMAN OTC DRUG LABEL
Date: 20240222

ACTIVE INGREDIENTS: NIACINAMIDE 0.04 g/100 mL
INACTIVE INGREDIENTS: WATER

ACTIVE INGREDIENT

Niacinamide,Adenosine,Biotin,Hexapeptide-2

INACTIVE INGREDIENT

Ultra-low molecular hyaluronic acid extract- 20%, Biotin-5%, Hexapeptide-2-5%, Natural organic sulfur((Garlic)-10%, Medicago sativa Fermented Extract-30%, Salix koreensis Andersson Fermented Extract-30%

PURPOSE

AUTOPHAGY is the process by which cells break down and recycle the irownun necessary cells or damaged components

Itplays an importantrole in keepingcells clean bydecomposing, differentiating,dividing, regulatinginflammatoryand immune responses

Keep out of reach of the children

INDICATIONS AND USAGE

After washing your face, take an appropriate amount and apply it to your skin, tap it to absorb it

WARNINGS

1. In the case of abnormal symptoms or side effects such as red spots, swelling, or itching due to direct sunlight during or after

use of cosmetics Consultation with a specialist, etc

2. Refrain from using it in areas with wounds, etc

3. Precautions for Storage and Handling

A. Keep it out of reach of children

B. Store away from direct sunlight

DOSAGE AND ADMINISTRATION

for external use only